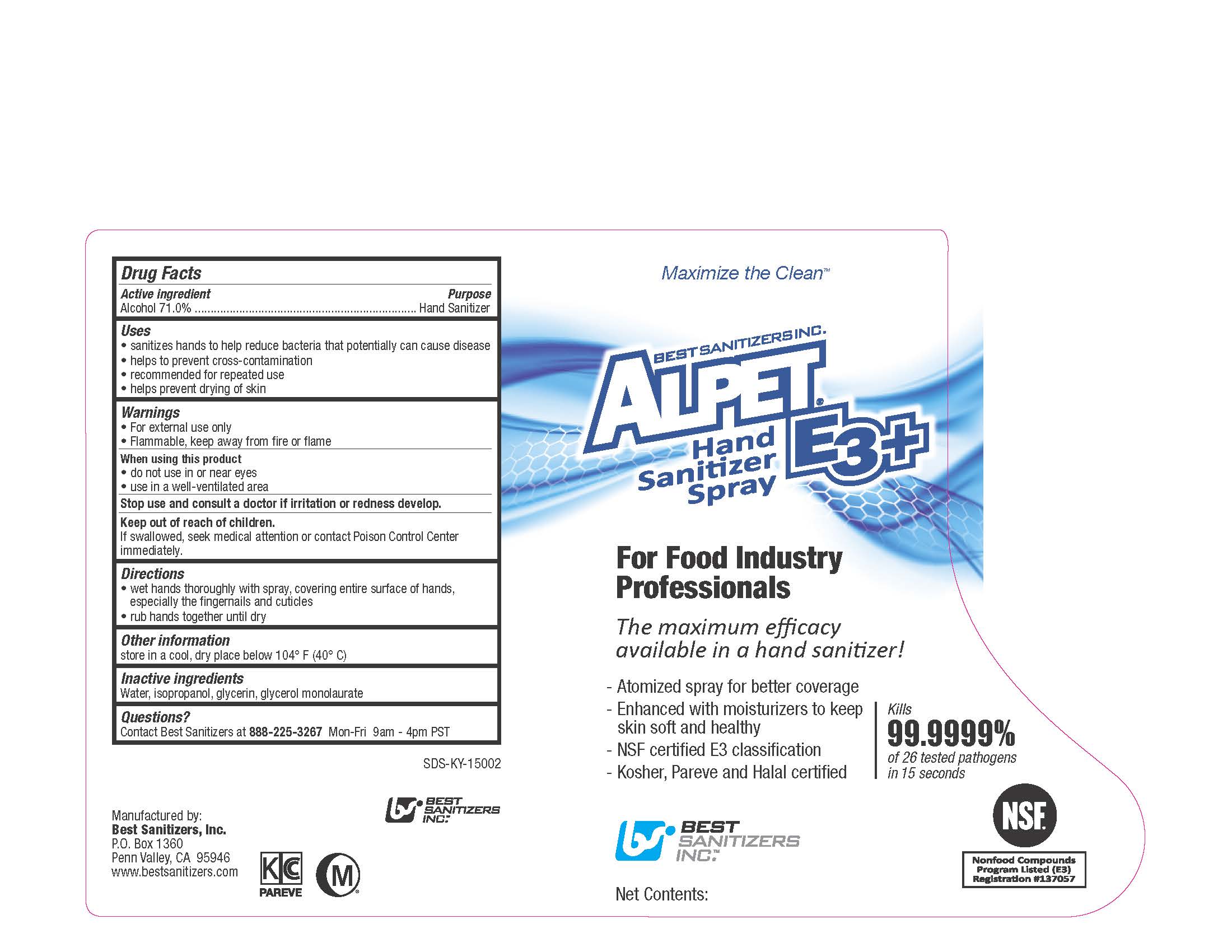 DRUG LABEL: ALPET E3 PLUS HAND SANITIZER
NDC: 59900-123 | Form: LIQUID
Manufacturer: Best Sanitizers, Inc.
Category: otc | Type: HUMAN OTC DRUG LABEL
Date: 20241205

ACTIVE INGREDIENTS: ALCOHOL 71 mL/100 mL
INACTIVE INGREDIENTS: WATER; ISOPROPYL ALCOHOL; GLYCERIN; GLYCERYL LAURATE

Drug Facts 59900-123

Active ingredient

Alcohol 71.0%

Purpose

Hand Sanitizer

Uses

- sanitizes hands to help reduce bacteria that potentially can cause disease

- helps to prevent cross-contamination

- recommended for repeated use

- helps prevent drying of skin

Warnings

- For external use only

- Flammable, keep away from fire or flame

When using this product

- do not use in or near eyes

- use in a well-ventilated area

Stop use and consult a doctor if irritation or redness develop.

Keep out of reach of children.

If swallowed, seek medical attention or contact Poison Control Center immediately.

Directions

- wet hands thoroughly with spray, covering entire surface of hands, especially the fingernails and cuticles

- rub hands together until dry

Other information

store in a cool, dry place below 104oF (40oC)

Inactive ingredients

Water, isopropanol, glycerin, glycerol monolaurate

Questions?

Contact Best Sanitizers at 888-225-3267Mon-Fri 9am - 4pm PST

PACKAGE LABEL

Maximize the Clean

BEST SANITIZERS INC.

ALPET E3 PLUS

Hand Sanitizer Spray

For Food Industry

Professionals

The maximum efficacy

available in a hand sanitizer!

Atomized spray for better coverage

Enhanced with moisturizers to keep

skin soft and healthy

NSF certified E3 classification

Kosher, Pareve and Halal certified

Kills

99.9999%

of 26 tested pathogens

in 15 seconds

BEST

SANITIZERS

INC.

NSF

Nonfood Compounds

Program Listed (E3)

Registration Number 137057

Net Contents: